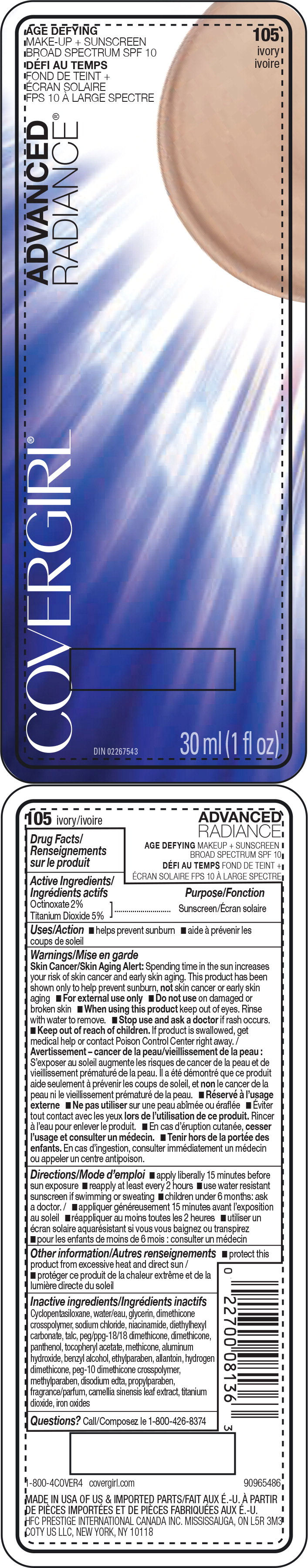 DRUG LABEL: Covergirl Advanced Radiance
NDC: 22700-098 | Form: LIQUID
Manufacturer: Noxell
Category: otc | Type: HUMAN OTC DRUG LABEL
Date: 20241119

ACTIVE INGREDIENTS: OCTINOXATE 20 mg/1 mL; TITANIUM DIOXIDE 50 mg/1 mL
INACTIVE INGREDIENTS: CYCLOMETHICONE 5; WATER; GLYCERIN; SODIUM CHLORIDE; DIMETHICONE CROSSPOLYMER (450000 MPA.S AT 12% IN CYCLOPENTASILOXANE); NIACINAMIDE; DIETHYLHEXYL CARBONATE; TALC; PEG/PPG-18/18 DIMETHICONE; DIMETHICONE; PANTHENOL; .ALPHA.-TOCOPHEROL ACETATE; METHICONE (20 CST); ALUMINUM HYDROXIDE; BENZYL ALCOHOL; ETHYLPARABEN; ALLANTOIN; HYDROGEN DIMETHICONE (20 CST); METHYLPARABEN; EDETATE DISODIUM ANHYDROUS; PROPYLPARABEN; GREEN TEA LEAF; FERRIC OXIDE RED

Covergirl Advanced Radiance®
Age Defying Makeup + Sunscreen SPF 10 (All shades)

Drug Facts

Active Ingredients

Octinoxate 2%
Titanium Dioxide 5%

Purpose

Sunscreen

Uses

- helps prevent sunburn

Warnings

Skin Cancer/Skin Aging Alert

Spending time in the sun increases your risk of skin cancer and early skin aging. This product has been shown only to help prevent sunburn, not skin cancer or early skin aging

- For external use only.

- Do not use on damaged or broken skin.

- When using this product keep out of eyes. Rinse with water to remove.

- Stop use and ask a doctor if rash occurs.

- Keep out of reach of children. If product is swallowed, get medical help or contact a Poison Control Center right away.

Directions

- apply liberally 15 minutes before sun exposure
- reapply at least every 2 hours
- use water resistant sunscreen if swimming or sweating
- children under 6 months: ask a doctor.

Other information

- protect this product from excessive heat and direct sun

Inactive ingredients

Cyclopentasiloxane, water/eau, glycerin, dimethicone crosspolymer, sodium chloride, niacinamide, diethylhexyl carbonate, talc, peg/ppg-18/18 dimethicone, dimethicone, panthenol, tocopheryl acetate, methicone, aluminum hydroxide, benzyl alcohol, ethylparaben, allantoin, hydrogen dimethicone, peg-10 dimethicone crosspolymer, methylparaben, disodium edta, propylparaben, fragrance/parfum, camellia sinensis leaf extract, titanium dioxide, iron oxides

Questions?

Call 1-800-426-8374

PRINCIPAL DISPLAY PANEL - 30 ml Bottle Carton

105
ivory

OLAY®
INGREDIENTS

COVERGIRL

ADVANCED RADIANCE®

age defying
makeup
+ sunscreen
SPF 10

DIN 02267543
30 ml (1 fl oz)